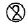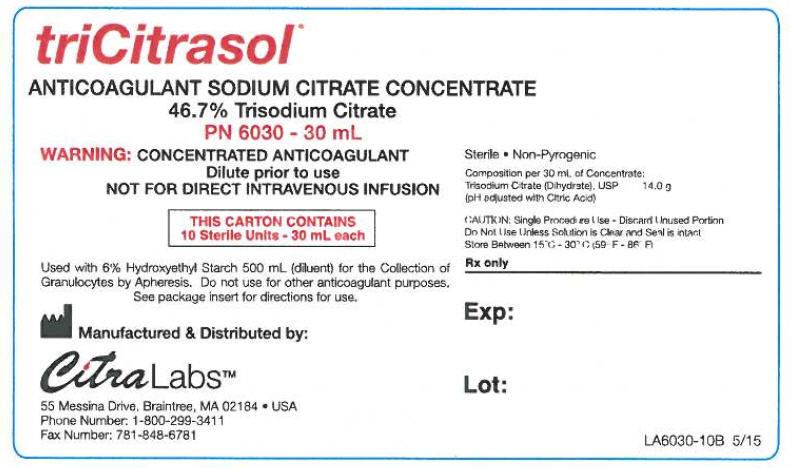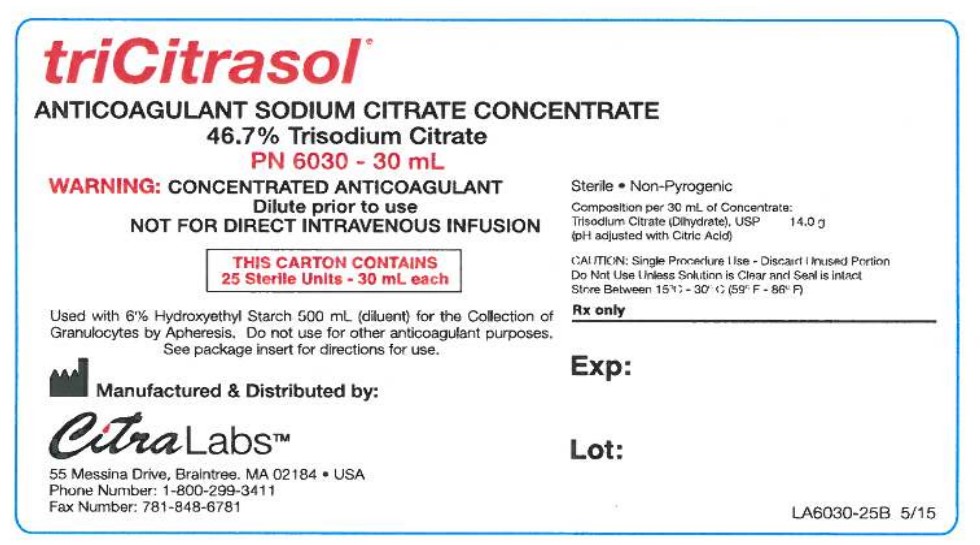 DRUG LABEL: triCitrasol
NDC: 23731-6030 | Form: SOLUTION
Manufacturer: Citra Labs LLC
Category: prescription | Type: HUMAN PRESCRIPTION DRUG LABEL
Date: 20230214

ACTIVE INGREDIENTS: TRISODIUM CITRATE DIHYDRATE 14 g/30 mL

triCitrasol®

ANTICOAGULANT SODIUM CITRATE CONCENTRATE – 46.7% Trisodium Citrate
PN 6030, 30 mL
NDC 23731-6030-3

DESCRIPTION

triCitrasol® Anticoagulant Sodium Citrate Concentrate, 46.7% Trisodium Citrate, is a sterile, non-pyrogenic solution of Trisodium Citrate (Dihydrate), USP.

Each 30 mL of concentrate contains:

Trisodium Citrate, dihydrate, USP | 14.0 grams
Water for Injection, USP | q.s.

pH adjusted with Citric Acid

pH: 6.3 – 6.6

Single patient use only, on a single occasion.

CLINICAL PHARMACOLOGY

A sodium citrate solution acts as an anticoagulant by the action of the citrate ion chelating free ionized calcium; thus, the calcium ion is unavailable to the coagulation system ^1.

INDICATIONS AND USAGE

triCitrasol® Anticoagulant Sodium Citrate Concentrate, 46.7% Trisodium Citrate, is an anticoagulant used in granulocytapheresis procedures (granulocyte collection by apheresis). Just prior to performing granulocytapheresis, aseptically add 30 mL of triCitrasol® to 500 mL of the 6% solution of Hydroxyethyl Starch (HES), e.g. Hespan ® 2-8. Agitate the resultant solution for 1 minute to assure a uniform concentration of anticoagulant. The resultant solution of triCitrasol® and 6% solution of HES contains the following concentration depending upon the volume used:

Volume of triCitrasol® | Volume of HES | Total Volume | Final Concentration of triCitrasol®
30 mL | 500 mL (measured from HES bag) | 530 mL | 2.6%
30 mL | 558 mL (injected directly into HES bag) | 588 mL | 2.4%

The triCitrasol®/HES solution is stable for up to 24 hours at room temperature after mixing.

Refer to the manufacturer's Operator's Manual of the apheresis medical device for the directions to perform the granulocytapheresis procedure.

CONTRAINDICATIONS

NOT FOR DIRECT INTRAVENOUS INFUSION.

WARNINGS

CONCENTRATED ANTICOAGULANT – DILUTE PRIOR TO USE.

PRECAUTIONS

General

Aseptic technique must be maintained at all times.

triCitrasol® Anticoagulant Sodium Citrate Concentrate is a clear/colorless solution. If the product shows any cloudiness or turbidity, the concentrate should be discarded.

The cap/stopper system provides a biological barrier and should be intact – discard product if system is comprised.

Information for Patients

None.

Laboratory Tests

There are no laboratory tests for the drug product at this time.

Drug Interactions

There are no adverse reactions for the addition of the product to the rouleaux agent.

Carcinogenesis, mutagenesis, impairment of fertility

Long-term studies in animals have not been performed to evaluate the carcinogenic potential of triCitrasol®.

Pregnancy

Long-term studies in animals have not been performed to evaluate the effects of triCitrasol® on pregnant women.

Pediatric Use

The safety and effectiveness of triCitrasol® in children have not been established.

ADVERSE REACTIONS

Citrate reactions or toxicity may occur with the infusion of blood products containing citrate anticoagulant ^(1. 9 11). The recipient of the citrated blood product should be monitored for the signs and symptoms of citrate toxicity ^(1. 9 11). The signs and symptoms of citrate toxicity begin with paresthesia, a "tingling" sensation around the mouth or in the extremities, followed by severe reactions that are characterized by chills, stomach cramps, or pressure in the chest, followed by more severe reactions that are characterized by hypotension and possible cardiac arrhythmia ^(1. 9 11). Citrate toxicity may occur more frequently in patients that are hypothermic ^10, have impaired liver or renal function ^10, or have low calcium levels because of an underlying disease ^9.

OVERDOSAGE

Since the bottle of triCitrasol® contains only 30mL of the product, it is impossible to overdose the addition of the product to the 6% solution of HES. However, in the event of a reaction to the infusion of citrated blood products, evaluate the patient and institute appropriate corrective actions ^(1, 9).

DOSAGE AND ADMINISTRATION

The apheresis system will control the amount of the citrate/6% solution of HES that is added to the whole blood and the method of administration of the solution. Refer to the Operator's Manual of the apheresis medical device.

HOW SUPPLIED

triCitrasol® Anticoagulant Sodium Citrate Concentrate 46.7% Trisodium Citrate

REF | SIZE | CASE
PN 6030-25 | 30 mL Vial | 25 Vials/Case
PN 6030-10 | 30 mL Vial | 10 Vials/Case

STORAGE AND HANDLING

It is recommended that the product be stored at ambient room temperature, 24°C (75°F); however, the product can be stored between 15°C (59°F) and 30°C (86°F). Protect from freezing and exposure to excessive heat should be minimized.

Rx ONLY

triCitrasol® is a registered trademark of Citra Labs, LLC, Braintree, MA.

Hespan ® is a registered trademark of B. Braun Medical, Inc., Irvine, CA.

REFERENCES

1. Grindon, A. J., "Adverse Reactions to Whole Blood Donation and Plasmapheresis", CRC Crit. Rev Clin. Lab. Sci., 17:51-75, 1982.
2. Rock, G., and McCombie, N., "Alternate Dosage Regimens for High-Molecular-Weight Hydroxyethyl Starch", Transfusion, 25:417-419, 1985.
3. Strauss, R. G., Hester, J. P., Vogler, W.R., Higby, D. J., Snikeris, A. C., Imig, K. M., Greazel, C., Mallard, G., Burnett, D., Gupta, S., and Hulse, J.D., "A Multicenter Trial to Document the Efficacy and Safety of a Rapidly Excreted Analog of Hydroxyethyl Starch for Leukapheresis with a Note on Steroid Stimulation of Granulocyte Donors", Transfusion, 26:258-264, 1986.
4. Strauss, R.G., Rohret, P.A., Randels, M. J., and Wihegarden, D. C., "Granulocyte Collection", J. of Clin. Apheresis, 6:241-243, 1991.
5. Lee, J.H., and Klein, H. G., "The Effect of Donor Red Cell Sedimentation Rate on Efficiency of Granulocyte Collection by Centrifugal Leukapheresis", Transfusion, 35:384-388, 1995.
6. Adkins, D., Ali., S. Despotis, G., Dynis, M. and Goodnough, L. T., "Granulocyte Collection Efficiency and Yield are Enhanced by the Use of a Higher Interface Offset During Apheresis of Donors Given Granulocyte-Colony-Stimulating Factor", Transfusion, 38:557-564, 1998.
7. Jendiroba, D. B., Lichtiger, B., Anaissie, E., Reddy, V., O'Brien, S., Kantarjian, H., and Freireich, E. J., "Evaluation and Comparison of Three Mobilization Methods for the Collection of Granulocytes". Transfusion, 38:722-728, 1998.
8. Leavey P. J., Thurman, G., and Anbruso, D. R., "Functional Characteristics of Neutrophils Collected and Stored After Administration of G-CSF", Transfusion. 40:414-419, 2000.
9. AABB Technical Manual, 14 th Edition, page 590, 2001.
10. Denlinger, J.V., Nahrwold, M. L., Gibbs, P.S., and Lecky, J.H., "Hypocalcemia During Rapid Blood Transfusion in Anaesthetized Man", Br. J. Anaesth., 48-995-1000, 1976.
11. Stack, G., Judge, J.V., and Snyder, E.L., "Febrile and Nonimmune Transfusion Reactions", in Principles of Transfusion Medicine, pp. 780-781, editors Rossi, E.C., Simon, T.L., Moss, G.S., and Gould, S.A., Williams & Wilkins, Baltimore, MD, 2 nd ed., 1996.

Manufactured & Distributed by: Citra Labs, LLC, 55 Messina Drive, Braintree, MA 02184 • 1-800-299-3411 or 1-781-848-2174 Fax: 1-781-848-6781

FL6030 04/13
Printed in USA

PRINCIPAL DISPLAY PANEL - 10 Vial Case Label

triCitrasol®

ANTICOAGULANT SODIUM CITRATE CONCENTRATE
46.7% Trisodium Citrate
PN 6030 - 30 mL
WARNING: CONCENTRATED ANTICOAGULANT
Dilute prior to use
NOT FOR DIRECT INTRAVENOUS INFUSION

THIS CARTON CONTAINS
10 Sterile Units - 30 mL each

Used with 6% Hydroxyethyl Starch 500 mL (diluent) for the Collection of
Granulocytes by Apheresis. Do not use for other anticoagulant purposes.
See package insert for directions for use.

Manufactured & Distributed by:
Citra Labs™
A Biomet Inc. Company.
55 Messina Drive, Braintree, MA 02184 ● USA
Phone Number: 1-800-299-3411
Fax Number: 781-848-6781

Sterile ■ Non-Pyrogenic

Composition per 30 mL of Concentrate:
Trisodium Citrate (Dihydrate), USP 14.0 g
(pH adjusted with Citric Acid)

CAUTION: Single Procedure Use - Discard Unused Portion
Do Not Use Unless Solution is Clear and Seal is intact
Store Between 15°C - 30° C (59° F - 86° F)

Rx only

Exp:

Lot:

LA6030-10B 5/15

PRINCIPAL DISPLAY PANEL - 25 Vial Case Label

triCitrasol®

ANTICOAGULANT SODIUM CITRATE CONCENTRATE
46.7% Trisodium Citrate
PN 6030 - 30 mL
WARNING: CONCENTRATED ANTICOAGULANT
Dilute prior to use
NOT FOR DIRECT INTRAVENOUS INFUSION

THIS CARTON CONTAINS
25 Sterile Units - 30 mL each

Used with 6% Hydroxyethyl Starch 500 mL (diluent) for the Collection of
Granulocytes by Apheresis. Do not use for other anticoagulant purposes.
See package insert for directions for use.

Manufactured & Distributed by:
Citra Labs™
A Biomet Inc. Company.
55 Messina Drive, Braintree, MA 02184 ● USA
Phone Number: 1-800-299-3411
Fax Number: 781-848-6781

Sterile ■ Non-Pyrogenic

Composition per 30 mL of Concentrate:
Trisodium Citrate (Dihydrate), USP 14.0 g
(pH adjusted with Citric Acid)

CAUTION: Single Procedure Use - Discard Unused Portion
Do Not Use Unless Solution is Clear and Seal is intact
Store Between 15°C - 30° C (59° F - 86° F)

Rx only

Exp:

Lot:

LA6030-25B 5/15